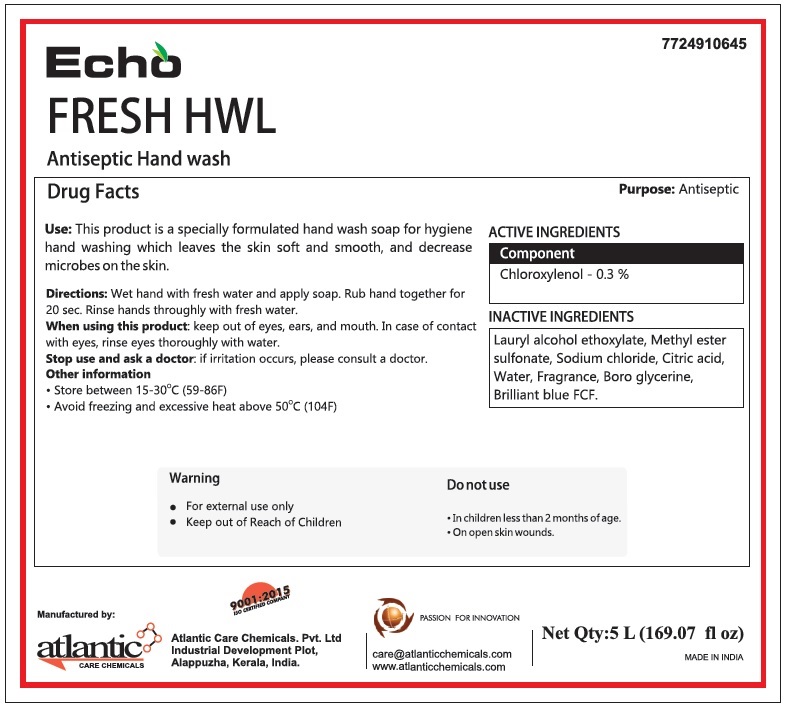 DRUG LABEL: Echo FRESH HWL Antiseptic Hand wash
NDC: 77249-106 | Form: LIQUID
Manufacturer: ATLANTIC CARE CHEMICALS PRIVATE LIMITED
Category: otc | Type: HUMAN OTC DRUG LABEL
Date: 20200522

ACTIVE INGREDIENTS: CHLOROXYLENOL 3 g/1 L
INACTIVE INGREDIENTS: LAURYL ALCOHOL; S-METHYL METHANETHIOSULFONATE; SODIUM CHLORIDE; CITRIC ACID MONOHYDRATE; WATER; BOROGLYCERIN; FD&C BLUE NO. 1

Echo FRESH HWL Antiseptic Hand wash

Purpose: Antispetic

ACTIVE INGREDIENTS

Component

Chloroxylenol - 0.3 %

INACTIVE INGREDIENTS

Lauryl alcohol ethoxylate, Methyl ester sulfonate, Sodium chloride, Citric acid, Water, Fragrance, Boro glycerine, Brilliant blue FCF

INDICATIONS AND USAGE

Use: This product is a specially formulated hand wash soap for hygiene hand washing which leaves the skin soft and smooth, and decrease microbes on the skin.

DOSAGE AND ADMINISTRATION

Directions: Wet hand with fresh water and apply soap. Rub hand together for 20 sec. Rinse hands thoroughly with fresh water.

When using this product: keep out of eyes, ears, and mouth. In case of contact with eyes, rinse eyes thoroughly with water.

Stop use and ask a doctor: if irritation occurs, please consult a doctor.

Do not use

• In children less than 2 months of age.

• On open skin wounds.

Warning

• For external use only

• Keep out of Reach of Children

Other information

• Store between 15-30°C (59-86F)

• Avoid freezing and excessive heat above 50°C (104F)

Manufactured by:
Atlantic Care Chemicals. Pvt. Ltd
Industrial Development Plot,
Alappuzha, Kerala, India.

9001:2015

ISO CERTIFIED COMPANY

PASSION FOR INNOVATION

care@atlanticchemicals.com
www.atlanticchemicals.com

MADE IN INDIA